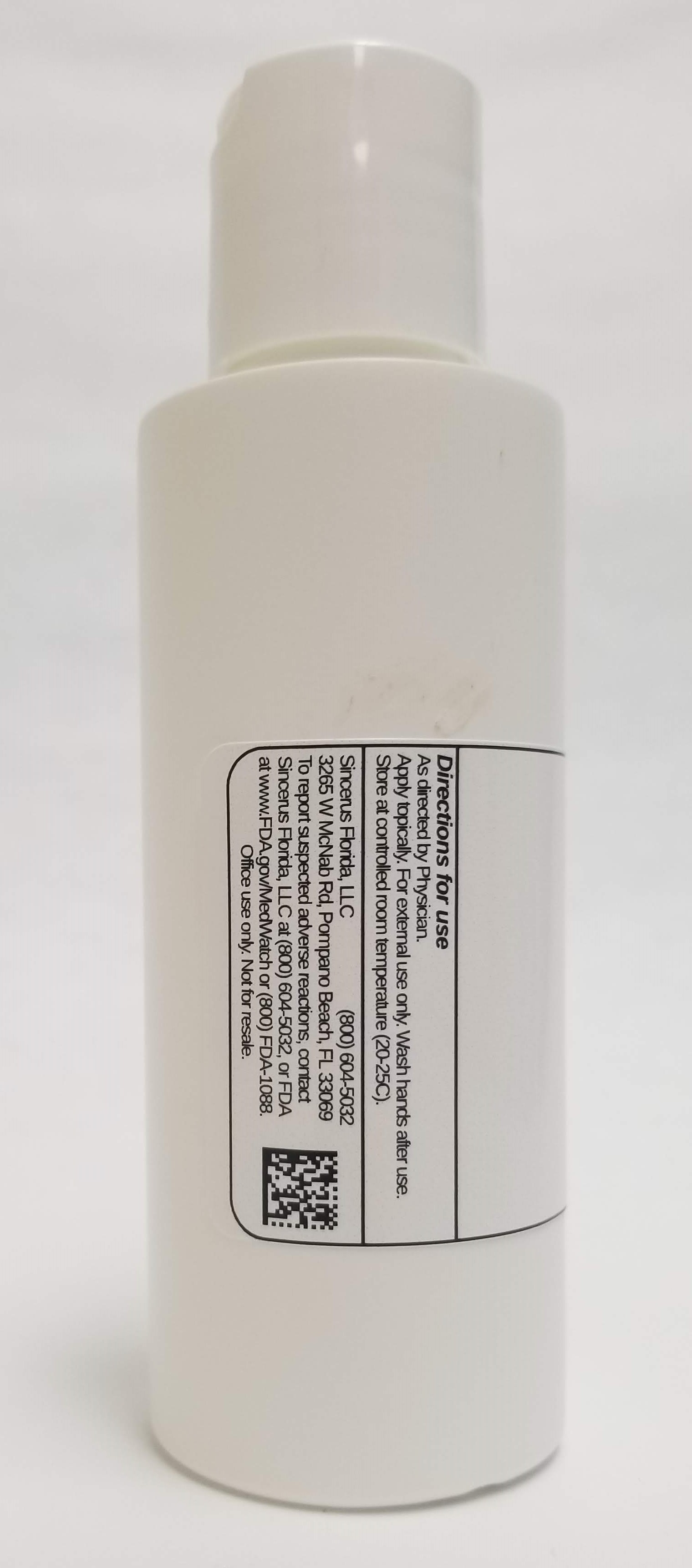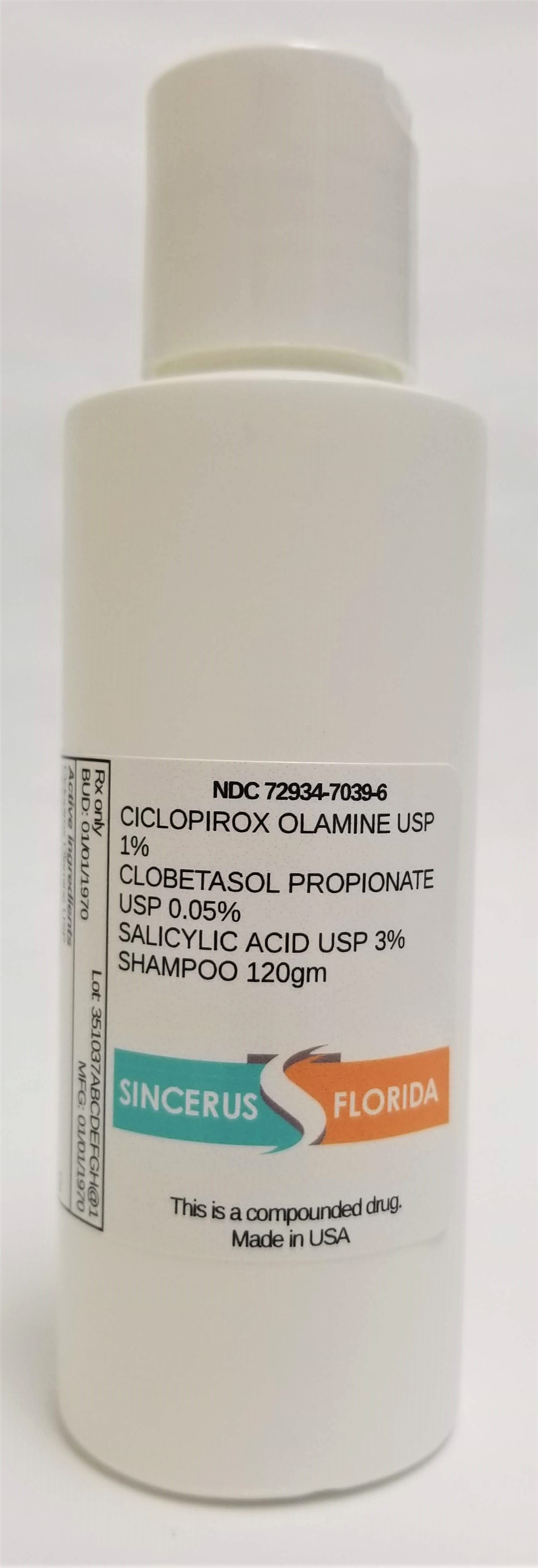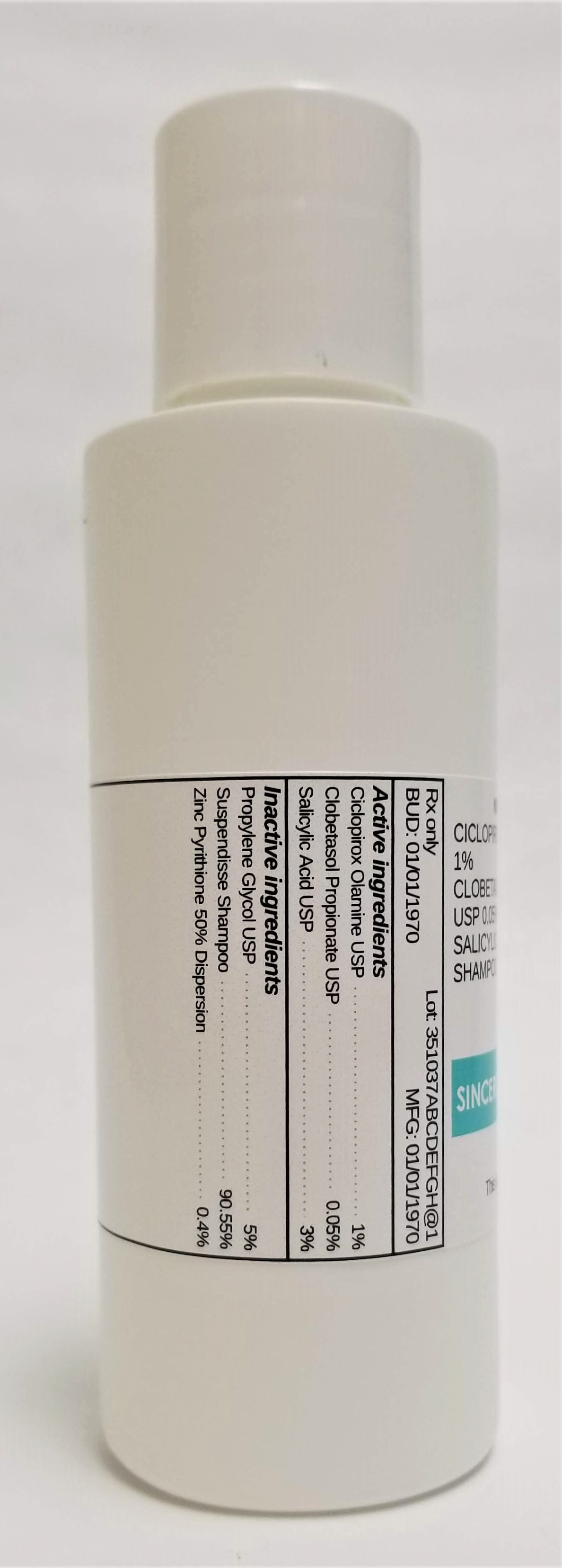 DRUG LABEL: CICLOPIROX OLAMINE 0.77% / CLOBETASOL PROPIONATE  0.05% / SALICYLIC ACID 3%.
NDC: 72934-7039 | Form: SHAMPOO
Manufacturer: Sincerus Florida, LLC
Category: prescription | Type: HUMAN PRESCRIPTION DRUG LABEL
Date: 20190516

ACTIVE INGREDIENTS: SALICYLIC ACID 3 g/100 g; CICLOPIROX OLAMINE 1 g/100 g; CLOBETASOL PROPIONATE 0.05 g/100 g

CICLOPIROX OLAMINE 0.77% / CLOBETASOL PROPIONATE 0.05% / SALICYLIC ACID 3%.